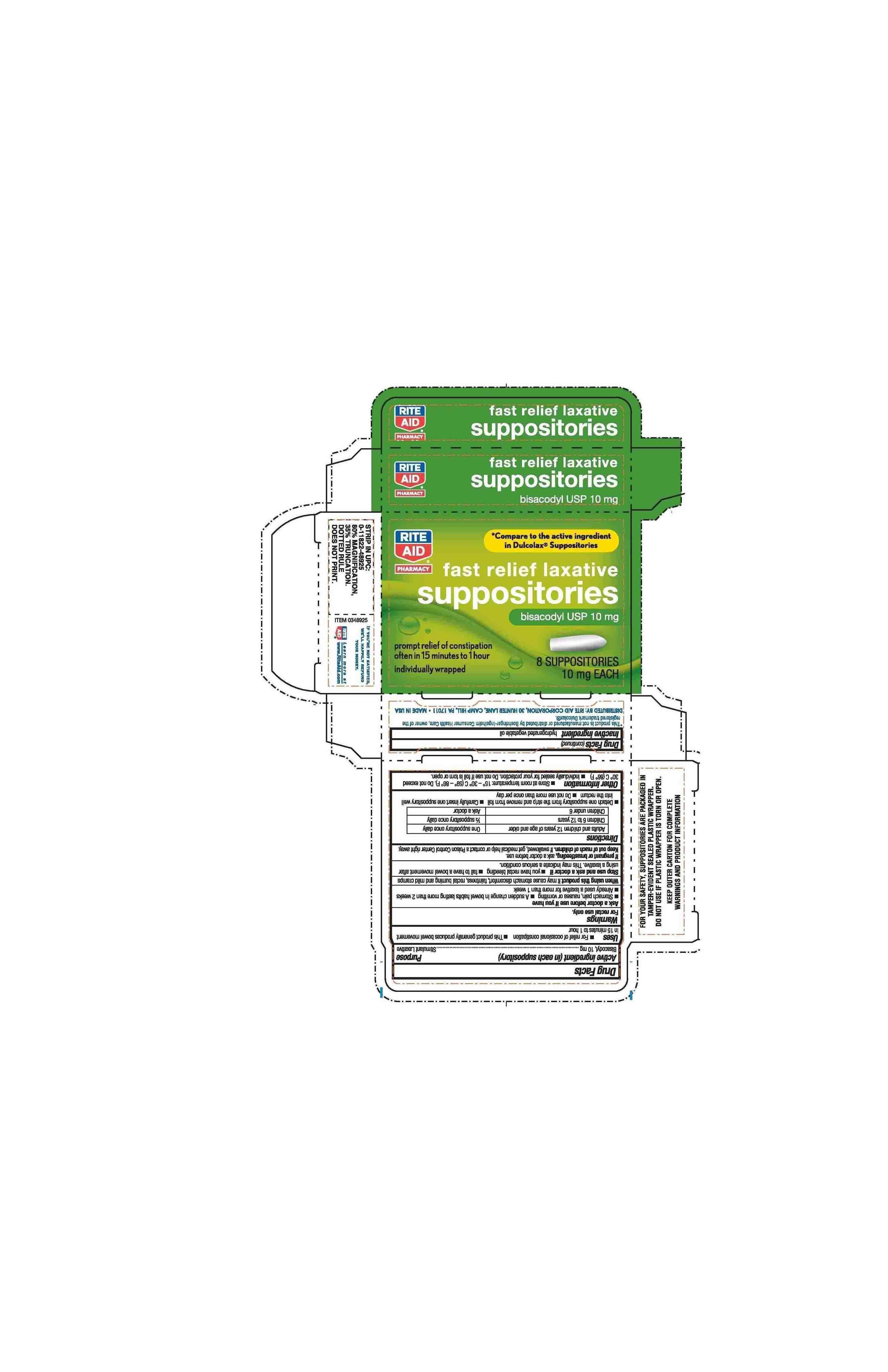 DRUG LABEL: Rite Aid fast relief laxative
NDC: 11822-4600 | Form: SUPPOSITORY
Manufacturer: Rite Aid Pharmacy
Category: otc | Type: HUMAN OTC DRUG LABEL
Date: 20211215

ACTIVE INGREDIENTS: BISACODYL 10 mg/2000 mg
INACTIVE INGREDIENTS: PALM KERNEL OIL 1990 mg/2000 mg

Rite-Aid® Bisacodyl Suppositories 8 ct.

Active Ingredient (in each Suppository) Purpose

Bisacodyl, 10 mg...................................Stimulant Laxative

Uses

Uses - For relief of occasional constipation -This product generally produces bowel movement in 15 minutes to 1 hour

Warnings

For rectal use only.

Ask a doctor before use if you have

-Stomach pain, nausea or vomiting -A sudden change in bowel habits lasting more than 2 weeks

-Already used a laxative more than 1 week

When using this product it may cause abdominal discomfort, faintness, rectal burning and mild cramps

Stop use and ask a doctor if -you have rectal bleeding -fail to have bowel movement after using a laxative. This may indicate a serious condition.

If pregnant or breast-feeding, ask a doctor before use.

Keep out of reach of children. If swallowed, get medical help or contact a Poison Control Center right away.

Directions

Adults and children 12 years of age and older One suppository once daily

Children 6 to 12 years 1/2 suppository once daily

Children under 6 Ask doctor

-Detach one suppository from the strip and remove from foil - Carefully insert one suppositry well into the rectum

-Do not use more than once per day

Other information

Other information - Store at room temperature: 15o - 30oC (59o - 86oF). Do not exceed 30oC (86oF) - Individually sealed for your protection. Do not use if foil is torn or open

Inactive ingredient

Inactive ingredient hydrogenated vegetable oil

Purpose

Active Ingredient (in each Suppository) Purpose
Bisacodyl, 10 mg...................................Stimulant Laxative